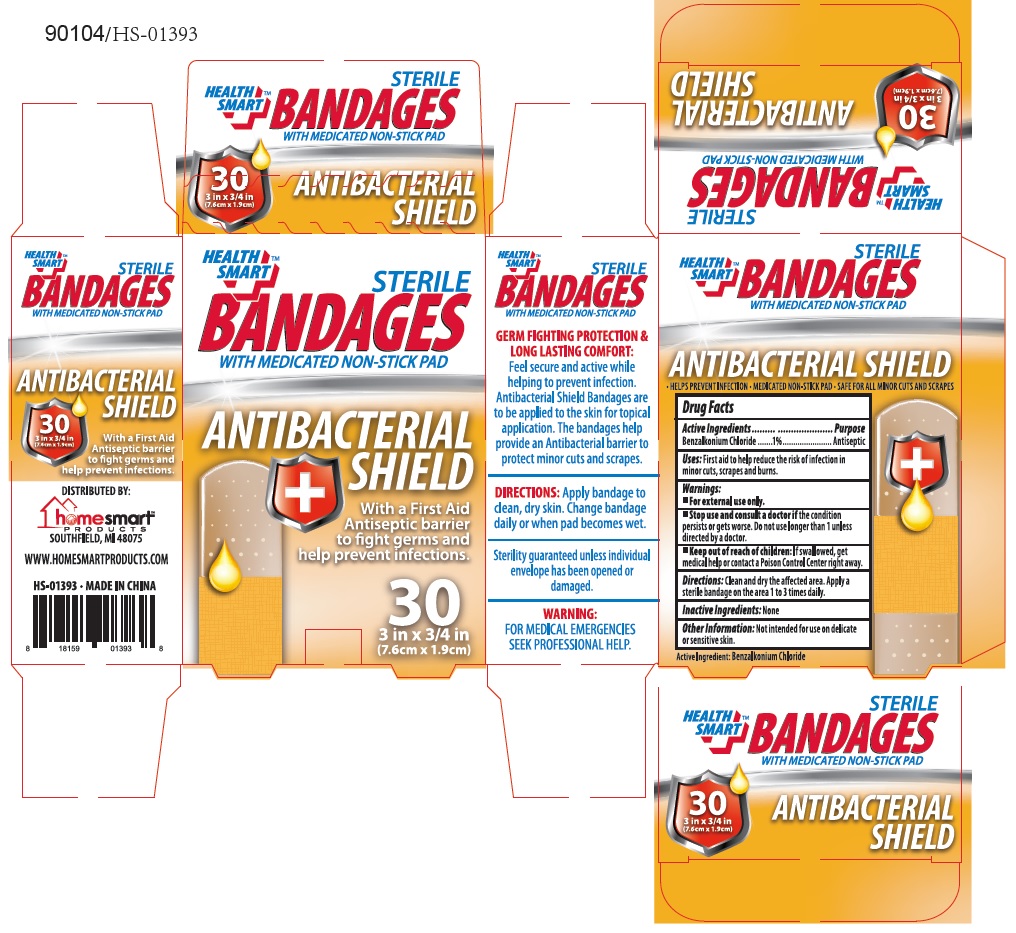 DRUG LABEL: ANTIBACTERIAL BANDAGE
NDC: 52862-313 | Form: SWAB
Manufacturer: International Wholesale, Inc.
Category: otc | Type: HUMAN OTC DRUG LABEL
Date: 20140923

ACTIVE INGREDIENTS: BENZALKONIUM CHLORIDE 1 g/100 g
INACTIVE INGREDIENTS: WATER

Active Ingredients

Benzalkonium Chloride 1 %

Purpose

Antiseptic

Use

First aid to help reduce the risk of infection in minor cuts, scrapes, and burns.

Warnings

For external use only.

Stop use and consult a doctor if the condition persists or gets worse. Do not use longer than 1 week unless directed by a doctor.

Keep out of reach of children: If swallowed, get medical help or contact Poison Control Center right away.

Directions

Clean and dry the affected area. Apply a sterile bandage on the area 1 to 3 times daily.

Inactive Ingredient

None

Other information: Not intended for use on delicate or sensitive skin.